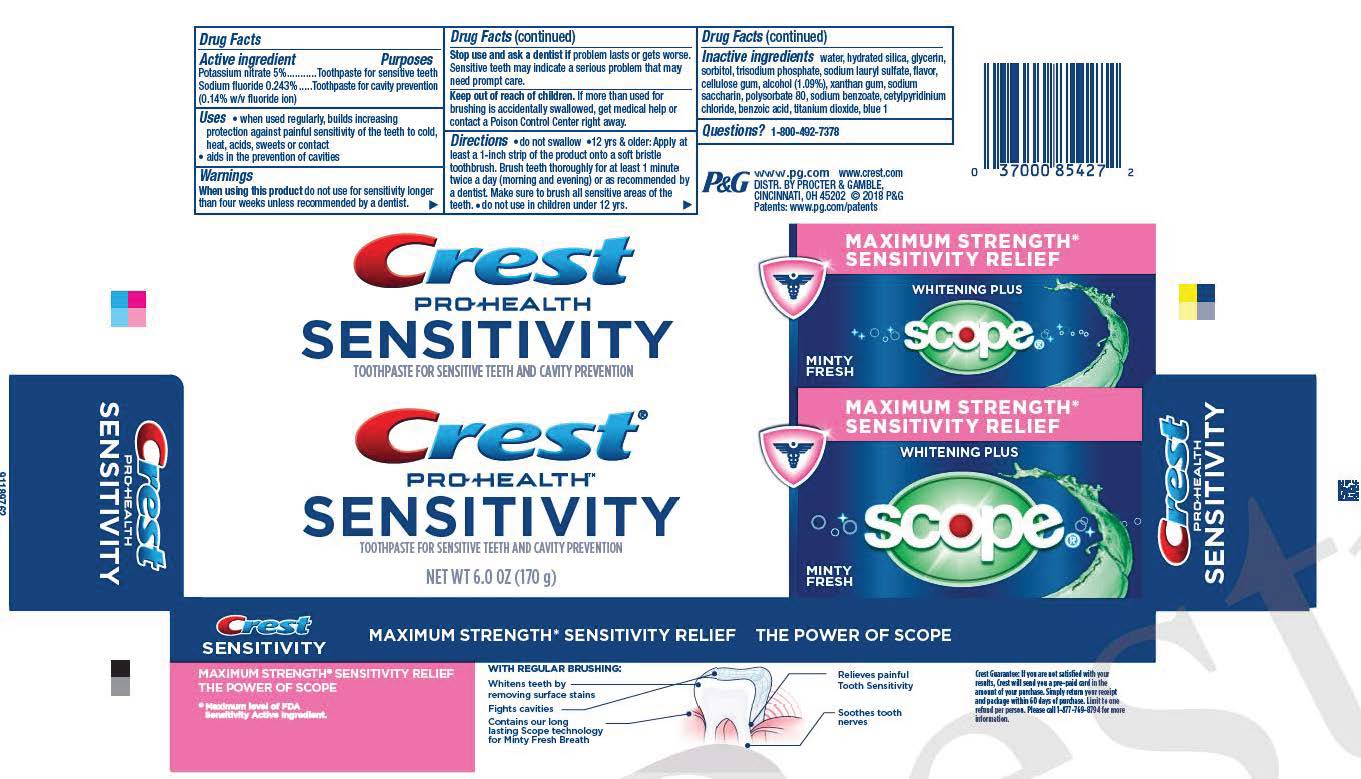 DRUG LABEL: Crest Pro-Health Sensitivity
NDC: 84126-622 | Form: PASTE, DENTIFRICE
Manufacturer: The Procter & Gamble Manufacturing Company
Category: otc | Type: HUMAN OTC DRUG LABEL
Date: 20260205

ACTIVE INGREDIENTS: POTASSIUM NITRATE 50 mg/1 g; SODIUM FLUORIDE 1.4 mg/1 g
INACTIVE INGREDIENTS: CETYLPYRIDINIUM CHLORIDE; BENZOIC ACID; TITANIUM DIOXIDE; FD&C BLUE NO. 1; SODIUM PHOSPHATE, TRIBASIC, ANHYDROUS; WATER; HYDRATED SILICA; GLYCERIN; SORBITOL; SODIUM LAURYL SULFATE; CARBOXYMETHYLCELLULOSE SODIUM; ALCOHOL; XANTHAN GUM; SACCHARIN SODIUM; POLYSORBATE 80; SODIUM BENZOATE

Crest Pro-Health Sensitivity Whitening Plus Scope

Drug Facts

ACTIVE INGREDIENT

Active ingredients | Purpose
Potassium nitrate 5% | Toothpaste for sensitive teeth
Sodium fluoride 0.243% (0.14% w/v fluoride ion) | Toothpaste for cavity prevention

Uses

- when used regularly, builds increasing protection against painful sensitivity of the teeth to cold, heat, acids, sweets or contact
- aids in the prevention of cavities

Warnings

WHEN USING

When using this productdo not use longer than four weeks unless recommended by a dentist.

Stop use and ask a dentist ifproblem lasts or gets worse. Sensitive teeth may indicate a serious problem that may need prompt care.

Keep out of reach of children.If more than used for brushing is accidentally swallowed, get medical help or contact a Poison Control Center right away.

Directions

- do not swallow
- 12 yrs. & older: Apply at least a 1-inch strip of the product onto a soft bristle toothbrush. Brush teeth thoroughly for at least 1 minute twice a day (morning and evening) or as recommended by a dentist. Make sure to brush all sensitive areas of the teeth.
- do not use in children under 12 yrs.

Inactive ingredients

water, hydrated silica, glycerin, sorbitol, trisodium phosphate, sodium lauryl sulfate, flavor, cellulose gum, alcohol 1.09%, xanthan gum, sodium saccharin, polysorbate 80, sodium benzoate, cetylpyridinium chloride, benzoic acid, titanium dioxide, blue 1

Questions?

1-800-492-7378

Dist. by Procter & Gamble, Cincinnati, OH 45202

PRINCIPAL DISPLAY PANEL - 170 g Tube Carton

Crest

PRO-HEALTH

SENSITIVITY

TOOTHPASTE FOR SENSITIVE TEETH AND CAVITY PROTECTION

NET WT 6.0 ZO 170 g)

MAXIMUM STRENGTH*

SENSITIVITY RELIEF

WHITENING PLUS

SCOPE

MINTY FRESH